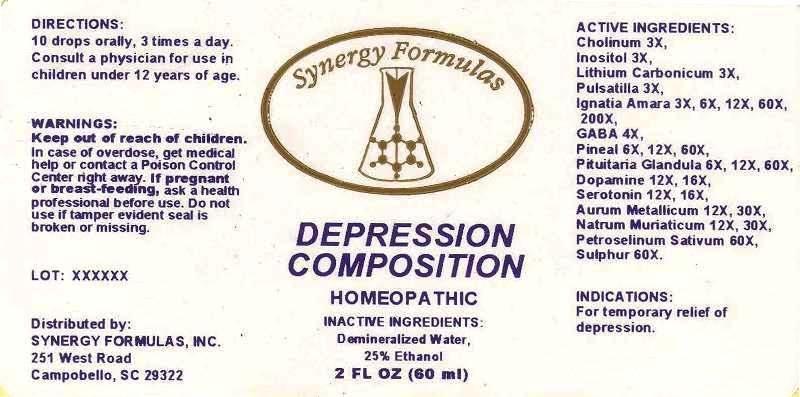 DRUG LABEL: DepressionComposition
NDC: 43772-0018 | Form: LIQUID
Manufacturer: Synergy Formulas, Inc.
Category: homeopathic | Type: HUMAN PRESCRIPTION DRUG LABEL
Date: 20130822

ACTIVE INGREDIENTS: CHOLINE HYDROXIDE 3 [hp_X]/1 mL; INOSITOL 3 [hp_X]/1 mL; LITHIUM CARBONATE 3 [hp_X]/1 mL; PULSATILLA VULGARIS 3 [hp_X]/1 mL; STRYCHNOS IGNATII SEED 3 [hp_X]/1 mL; .GAMMA.-AMINOBUTYRIC ACID 4 [hp_X]/1 mL; SUS SCROFA PITUITARY GLAND 6 [hp_X]/1 mL; SUS SCROFA PINEAL GLAND 6 [hp_X]/1 mL; DOPAMINE 12 [hp_X]/1 mL; SEROTONIN 12 [hp_X]/1 mL; GOLD 12 [hp_X]/1 mL; SODIUM CHLORIDE 12 [hp_X]/1 mL; PETROSELINUM CRISPUM 60 [hp_X]/1 mL; SULFUR 60 [hp_X]/1 mL
INACTIVE INGREDIENTS: WATER; ALCOHOL

DRUG FACTS:

ACTIVE INGREDIENTS:

Cholinum 3X, Inositol 3X, Lithium Carbonicum 3X, Pulsatilla 3X, Ignatia Amara 3X, GABA 4X, Pituitaria Glandula (Suis) 6X, 12X, 60X, Pineal (Suis) 6X, 12X, 60X, Dopamine 12X, 16X, Serotonin 12X, 16X, Aurum Metallicum 12X, 30X, Natrum Muriaticum 12X, 30X, Petroselinum Sativum 60X, Sulphur 60X.

INDICATIONS:

For temporary relief of depression.

WARNINGS:

Keep out of reach of children. In case of overdose, get medical help or contact a Poison Control Center right away.

If pregnant or breast-feeding, ask a health professional before use.

Do not use if tamper evident seal is broken or missing.

DIRECTIONS:

10 drops orally, 3 times a day. Consult a physician for use in children under 12 years of age.

INACTIVE INGREDIENTS:

Demineralized Water, 25% Ethanol

Keep out of reach of children. In case of overdose, get medical help or contact a Poison Control Center right away.

INDICATIONS:

For temporary relief of depression.

QUESTIONS:

Distributed by:

SYNERGY FORMULAS, INC.

251 West Road

Campobello, SC 29322

PACKAGE DISPLAY LABEL:

Synergy Formulas
DEPRESSION COMPOSITION
HOMEOPATHIC
2 FL OZ (60 mL)